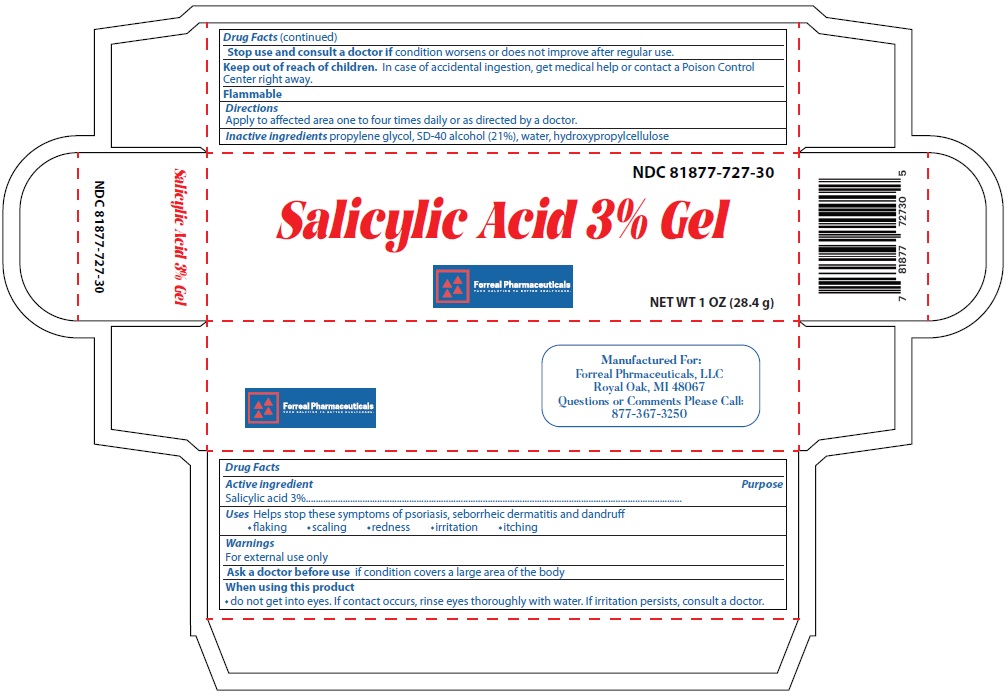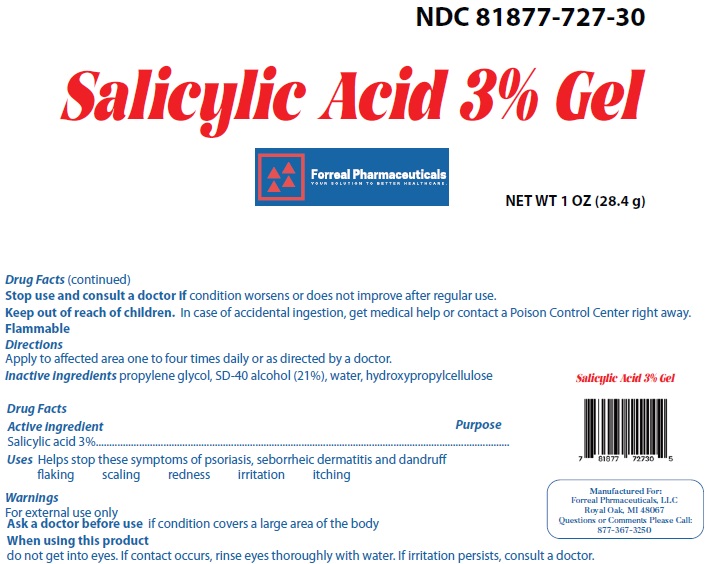 DRUG LABEL: Salicyclic Acid 3% Gel
NDC: 81877-727 | Form: GEL
Manufacturer: FORREAL PHARMACEUTICALS LLC 
Category: otc | Type: HUMAN OTC DRUG LABEL
Date: 20250919

ACTIVE INGREDIENTS: SALICYLIC ACID 3 g/100 g
INACTIVE INGREDIENTS: PROPYLENE GLYCOL; ALCOHOL; HYDROXYPROPYL CELLULOSE (1600000 WAMW); WATER

ACTIVE INGREDIENT

Forreal Pharmaceuticals, LLC - SALICYLIC ACID 3% GEL

ACTIVE INGREDIENT

SALICYLIC ACID 3%

PURPOSE

PSORIASIS, SEBORRHEIC DERMATITIS

USES

HELPS STOP THESE SYMPTOMS OF PSORIASIS, SEBORRHEIC DERMATITIS AND DANDRUFF

- FLAKING
- SCALING
- REDNESS
- IRRITATION
- ITCHING

WARNINGS

FOR EXTERNAL USE ONLY

ASK A DOCTOR BEFORE USE IF CONDITION COVERS A LARGE AREA OF THE BODY

WHEN USING THIS PRODUCT

- DO NOT GET INTO EYES. IF CONTACT OCCURS, RINSE EYES THOROUGHLY WITH WATER. IF IRRITATION PERSISTS, CONSULT A DOCTOR.

STOP USE AND CONSULT A DOCTOR IF CONDITION WORSENS OR DOES NOT IMPROVE AFTER REGULAR USE.

KEEP OUT OF REACH OF CHILDREN. IN CASE OF ACCIDENTAL INGESTION, GET MEDICAL HELP OR CONTACT A POISON CONTROL CENTER RIGHT AWAY.

FLAMMABLE

DIRECTIONS

- APPLY TO AFFECTED AREA ONE TO FOUR TIMES DAILY OR AS DIRECTED BY A DOCTOR.

INACTIVE INGREDIENTS

PROPYLENE GLYCOL, SD-40 ALCOHOL (21%), WATER, HYDROXYPROPYLCELLULOSE

PRINCIPAL DISPLAY PANEL

NDC 81877-727-30

Salicylic Acid 3% Gel

Forreal Pharmaceuticals
YOUR SOLUTION TO BETTER HEALTHCARE.

NET WT 1 OZ (28.4 g)

PRINCIPAL DISPLAY PANEL

NDC 81877-727-30

Salicylic Acid 3% Gel

Forreal Pharmaceuticals
YOUR SOLUTION TO BETTER HEALTHCARE.

NET WT 1 OZ (28.4 g)